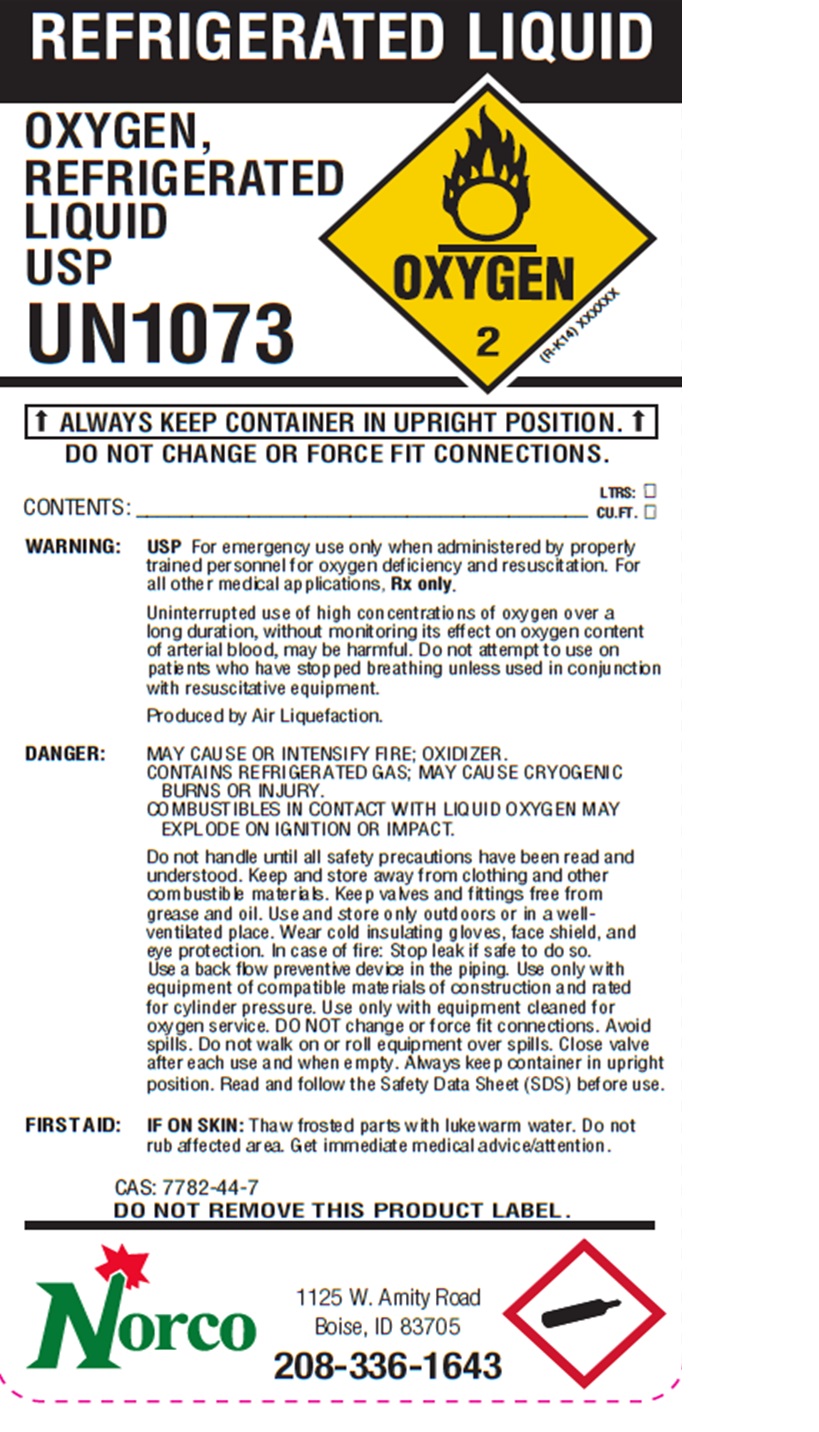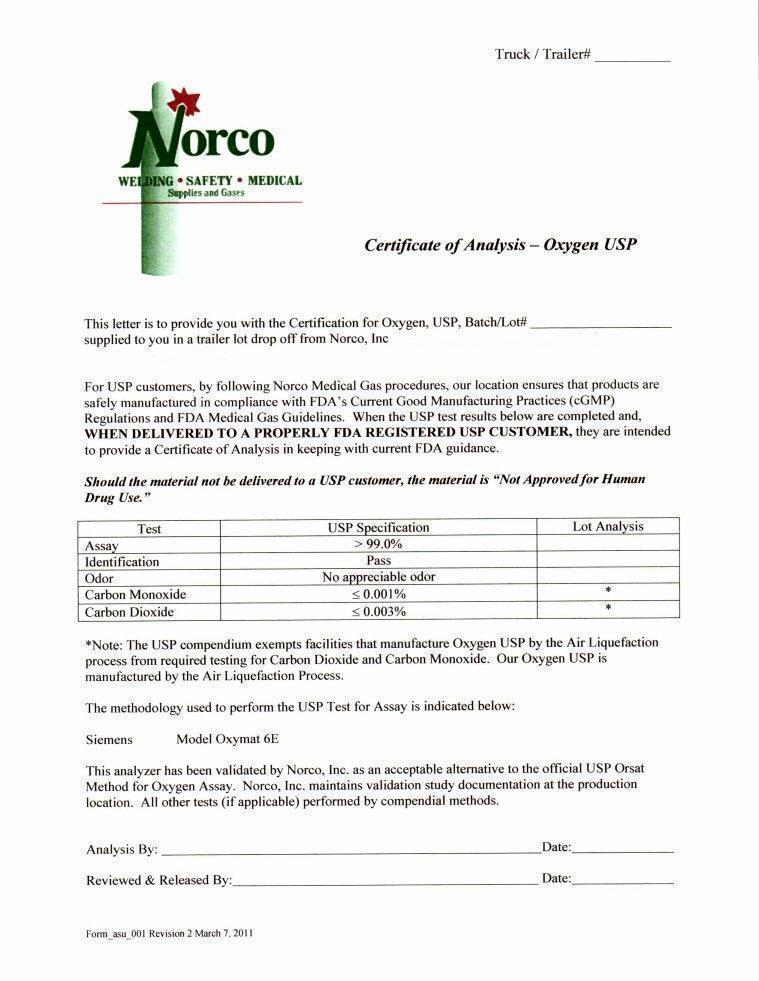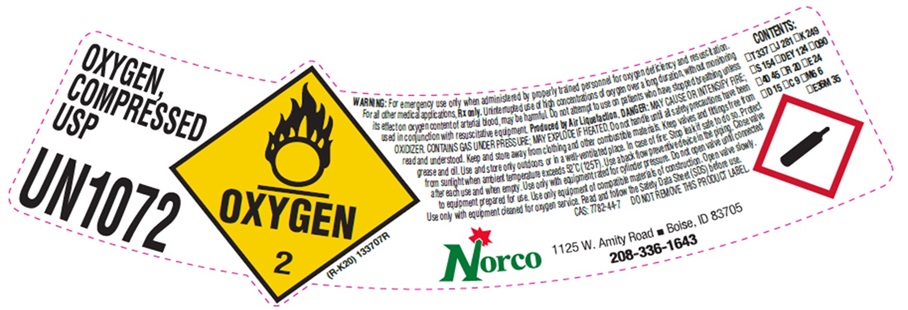 DRUG LABEL: OXYGEN
                
                
NDC: 42602-001 | Form: GAS
Manufacturer: Norco, Inc.
Category: prescription | Type: HUMAN PRESCRIPTION DRUG LABEL
Date: 20251212

ACTIVE INGREDIENTS: OXYGEN 999 L/1000 L

OXYGEN COMPRESSED USP LABEL

OXYGEN,
COMPRESSED USP
UN1072
OXYGEN 2 (R-K20) 133707R

WARNING: For emergency use only when administered by properly trained personnel for oxygen deficiency and resuscitation.
For all other medical applications, Rx only. Uninterrupted use of high concentrations of oxygen over a long duration, without monitoring
its effect on oxygen content of arterial blood, may be harmful. Do not attempt to use on patients who have stopped breathing unless
used in conjunction with resuscitative equipment. Produced by Air Liquefaction. DANGER: MAY CAUSE OR INTENSIFY FIRE;
OXIDIZER. CONTAINS GAS UNDER PRESSURE; MAY EXPLODE IF HEATED. Do not handle until all safety precautions have been
read and understood. Keep and store away from clothing and other combustible materials. Keep valves and fittings free from
grease and oil. Use and store only outdoors or in a well-ventilated place. In case of fire: Stop leak if safe to do so. Protect
from sunlight when ambient temperature exceeds 52 C (125 F). Use a back flow preventive device in the piping. Close valve
after each use and when empty. Use only with equipment rated for cylinder pressure. Do not open valve until connected
to equipment prepared for use. Use only equipment of compatible materials of construction. Open valve slowly.
Use only with equipment cleaned for oxygen service. Read and follow the Safety Data Sheet (SDS) before use.

CAS: 7782-44-7
DO NOT REMOVE THIS PRODUCT LABEL

Norco 1125 W. Amity Road • Boise, ID 83705
208-336-1643

CONTENTS
__T 337 __ J 281 __K 249
__S 154 __DEY 124 __Q 90
__40 45 __R 20 __E 24
__D 15 __C 9 __M6 6
__E36M 35

res

OXYGEN REFRIGERATED LIQUID LABEL

REFRIGERATED LIQUID
OXYGEN
REFRIGERATED
LIQUID
USP
UN1073
OXYGEN 2 (R-K14) XXXXXX

↑ ALWAYS KEEP CONTAINER IN UPRIGHT POSITION. ↑
DO NOT CHANGE OR FORCE FIT CONNECTIONS.

LTRS: __
CONTENTS: ______________________________________ CU.FT. __

WARNING: USP For emergency use only when administered by properly
trained personnel for oxygen deficiency and resuscitation. For
all other medical applications. Rx only.

Uninterrupted use of high concentrations of oxygen over a
long duration, without monitoring its effect on oxygen content
of arterial blood, may be harmful. Do not attempt to use on
patients who have stopped breathing unless used in conjunction
with resuscitative equipment.

Produced by Air Liquefaction.

DANGER: MAY CAUSE OR INTENSIFY FIRE; OXIDIZER.
CONTAINS REFRIGERATED GAS; MAY CAUSE CRYOGENIC
BURNS OR INJURY.
COMBUSTIBLES IN CONTACT WITH LIQUID OXYGEN MAY
EXPLODE ON IGNITION OR IMPACT.

Do not handle until all safety precautions have been read and
understood. Keep and store away from clothing and other
combustible materials. Keep valves and fittings free from
grease and oil. Use and store only outdoors or in a well-
ventilated place. Wear cold insulating gloves, face shield, and
eye protection. In case of fire: Stop leak if safe to do so.
Use a back flow preventive device in the piping. Use only with
for cylinder pressure. Use only with equipment cleaned for
oxygen service. DO NOT change or force fit connections. Avoid
spills. Do not walk on or roll equipment over spills. Close valve
after each use and when empty. Always keep container in upright
position. Read and follow the Safety Data Sheet (SDS) before use.

FIRST AID: IF ON SKIN: Thaw frosted parts with lukewarm water. Do not
rub affected area. Get immediate medical advice/attention.

CAS: 7782-44-7
DO NOT REMOVE THIS PRODUCT LABEL

Norco 1125 W. Amity Road
Boise, ID 83705
208-336-1643

res